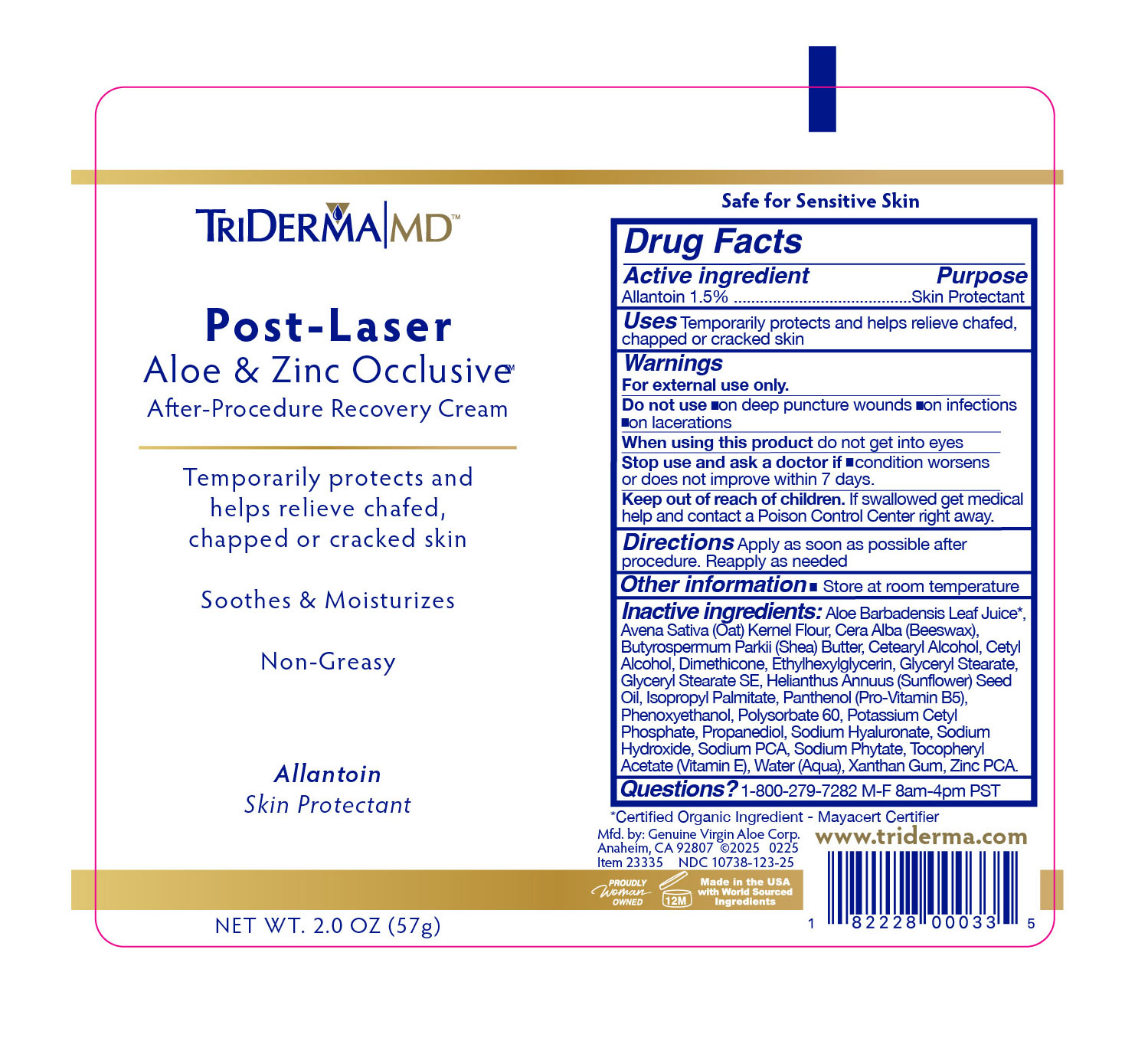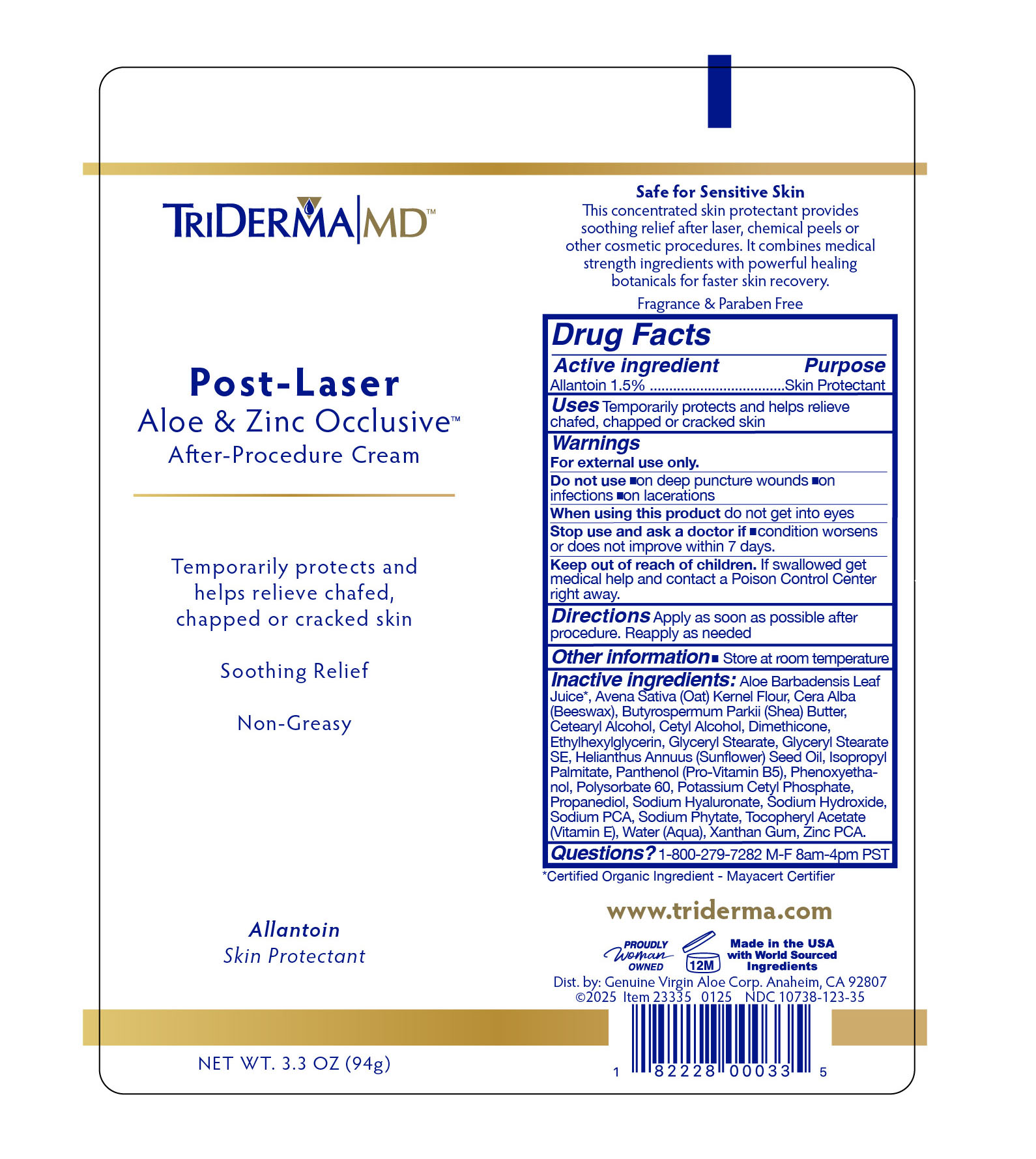 DRUG LABEL: TriDerma Aloe Zinc Occlusive
NDC: 10738-123 | Form: CREAM
Manufacturer: Genuine Virgin Aloe Corporation
Category: otc | Type: HUMAN OTC DRUG LABEL
Date: 20260130

ACTIVE INGREDIENTS: ALLANTOIN 1.5 g/100 g
INACTIVE INGREDIENTS: DIMETHICONE 100; BEESWAX; ALOE VERA LEAF JUICE; SHEA BUTTER

TriDerma Post Laser Aloe Zinc Occlusive

PURPOSE

Skin Protectant

DIRECTIONS

Apply as soon as possible after procedure. Reapply as often as needed.

INACTIVE INGREDIENTS

Aloe Barbadensis Leaf Juice*,
Avena Sativa (Oat) Kernel Flour, Cera Alba (Beeswax),
Butyrospermum Parkii (Shea) Butter, Cetearyl Alcohol, Cetyl
Alcohol, Dimethicone, Ethylhexylglycerin, Glyceryl Stearate,
Glyceryl Stearate SE, Helianthus Annuus (Sunflower) Seed
Oil, Isopropyl Palmitate, Panthenol (Pro-Vitamin B5),
Phenoxyethanol, Polysorbate 60, Potassium Cetyl
Phosphate, Propanediol, Sodium Hyaluronate, Sodium
Hydroxide, Sodium PCA, Sodium Phytate, Tocopheryl
Acetate (Vitamin E), Water (Aqua), Xanthan Gum, Zinc PCA.

*Certified Organic Ingredient - Mayacert Certifier

WARNINGS

For external use only

ACTIVE INGREDIENT

Allantoin 1.5%

USES

temporarily protects and helps relieved chafed, chapped or cracked skin.

DO NOT USE:

on deep puncture wounds, on infections, on lacerations

WHEN USING THIS PRODUCT:

do not get into eyes

KEEP OUT OF REACH OF CHILDREN

if swallowed get medical help and contact a Poison Control Center right away.

STOP USE AND ASK A DOCTOR IF:

condition worsens or does not improve within 7 days.